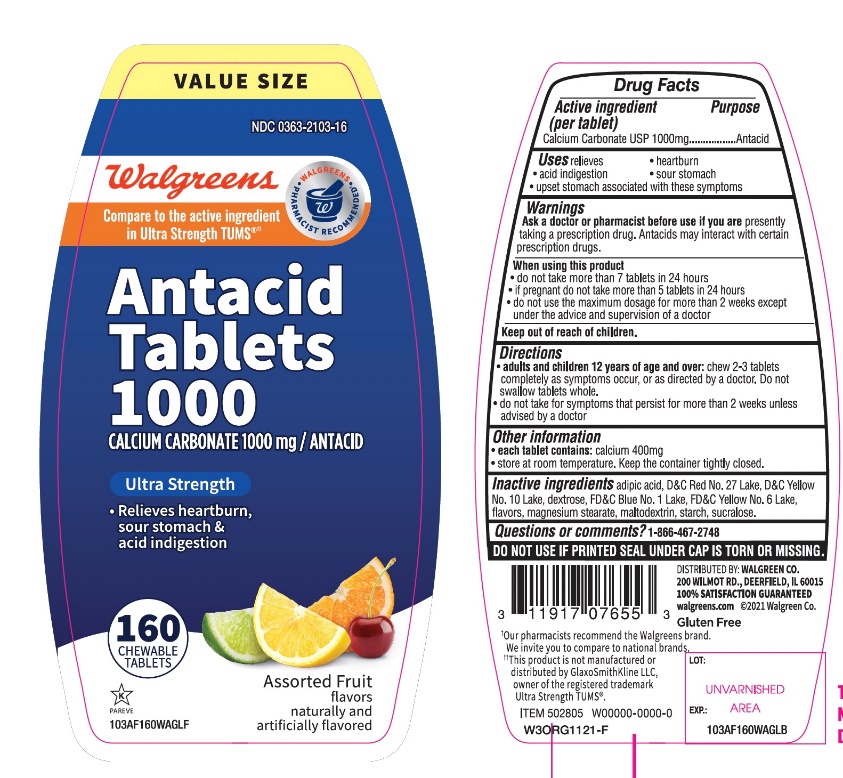 DRUG LABEL: Antacid Ultra Strength

NDC: 0363-2103 | Form: TABLET, CHEWABLE
Manufacturer: WALGREEN CO.
Category: otc | Type: HUMAN OTC DRUG LABEL
Date: 20251125

ACTIVE INGREDIENTS: CALCIUM CARBONATE 1000 mg/1 1
INACTIVE INGREDIENTS: ADIPIC ACID; D&C RED NO. 27; D&C YELLOW NO. 10; DEXTROSE, UNSPECIFIED FORM; FD&C BLUE NO. 1; FD&C YELLOW NO. 6; MAGNESIUM STEARATE; MALTODEXTRIN; STARCH, CORN; SUCRALOSE

Walgreens Antacid Tablets 1000 Calcium Carbonate 1000 mg Ultra Strength Assorted fruits Flavor 160 Chewable Tablets

Active ingredient (per tablet)

Calcium Carbonate USP 1000 mg

Purpose

Antacid

Uses

relieves

• heartburn

• sour stomach

• acid indigestion

• upset stomach associated with these symptoms

Warnings

Ask a doctor or pharmacist before use if you arepresently taking a prescription drug. Antacids may interact with certain prescription drugs.

When using this product

- do not take more than 7 tablets in 24 hours
- if pregnant do not take more than 5 tablets in 24 hours
- do not use the maximum dosage for more than 2 weeks except under the advice and supervision of a doctor.

Directions

- adults and children 12 years of age and over:chew 2-3 tablets completely as symptoms occur, or as directed by a doctor. Do not swallow tablets as whole.
- do not take for symptoms that persist for more than 2 weeks unless advised by a doctor

Other information

- each tablet contains:elemental calcium 400 mg
- store at room temperature. Keep the container tightly closed

Inactive ingredients

adipic acid, D&C red 27,D&C yellow10, dextrose, FD&C blue 1,FD&C yellow 6, flavors, magnesium stearate, maltodextrin, , starch, sucralose.

Questions or comments?

1-866-467-2748

Safety sealed: Do not use if printed seal under cap is torn or missing

Package/Label Principal Display Panel

Walgreens

Compare to TUMS®active ingredient††

NDC 0363-2103-16

Antacid Tablets 1000

CALCIUM CARBONATE 1000mg/ ANTACID

ULTRA STRENGTH

- Relieves heartburn, sour stomach & acid indigestion

ASSORTED FRUIT FLAVORS

160 CHEWABLE TABLETS

GLUTEN-FREE

Walgreens Pharmacist Recommended

Walgreens Pharmacist Survey

††This product is not manufactured or distributed by GlaxoSmithKline, the distributer of TUMS®

DISTRIBUTED BY: WALGREEN CO.

200 WILMOT RD., DEERFIELD, IL 60015

100 % SATISFACTION GUARANTEED

walgreens.com ©2017 Walgreen Co.

ITEM502805

ORG1217-F

REV 0119